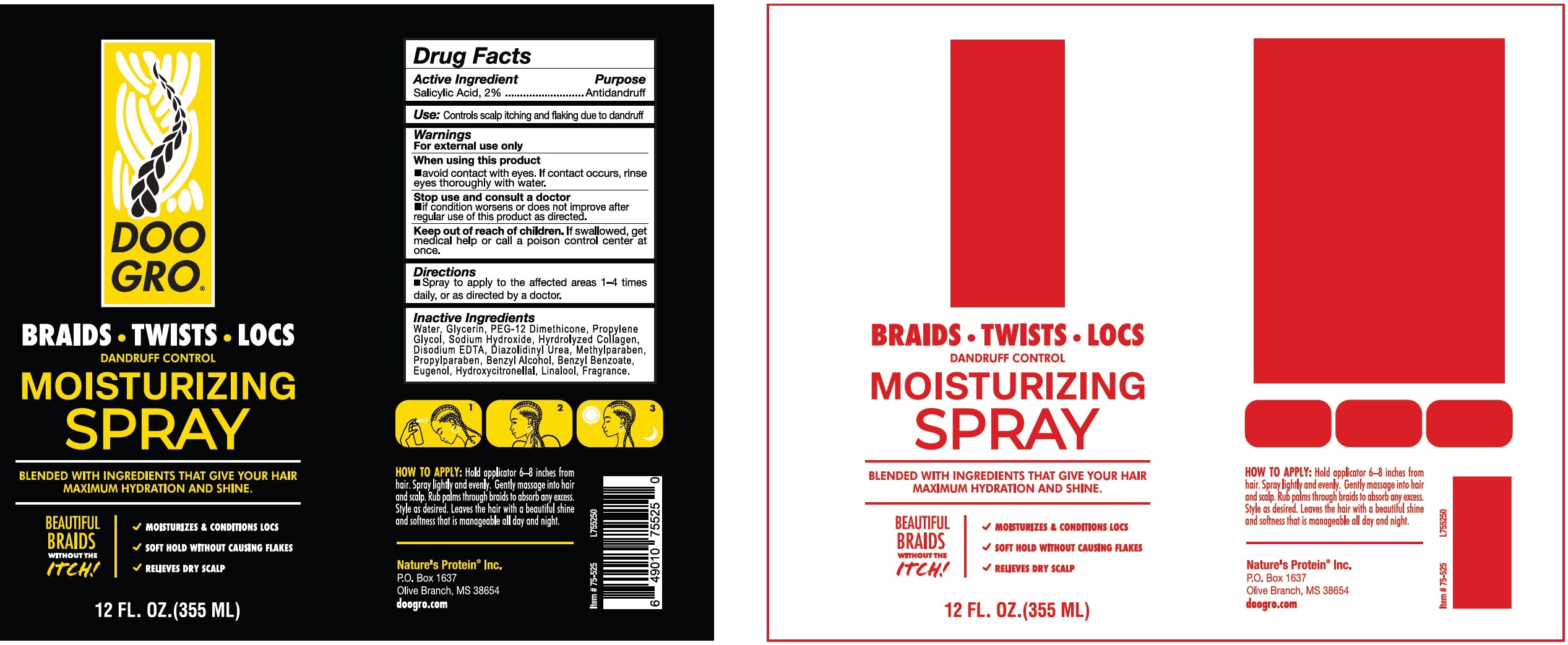 DRUG LABEL: Doo Gro Braids Twists Locs Dandruff Control Moisturizing
NDC: 12022-041 | Form: LIQUID
Manufacturer: J. Strickland and Co.
Category: otc | Type: HUMAN OTC DRUG LABEL
Date: 20240215

ACTIVE INGREDIENTS: SALICYLIC ACID 20 mg/1 mL
INACTIVE INGREDIENTS: WATER; GLYCERIN; PEG-12 DIMETHICONE; PROPYLENE GLYCOL; SODIUM HYDROXIDE; EDETATE DISODIUM; DIAZOLIDINYL UREA; METHYLPARABEN; PROPYLPARABEN; BENZYL ALCOHOL; BENZYL BENZOATE; EUGENOL; HYDROXYCITRONELLAL; LINALOOL, (+/-)-

Doo Gro Braids Twists Locs Dandruff Control Moisturizing Spray

Active Ingredient

Salicylic Acid, 2%

Purpose

Antidandruff

Use:

Controls scalp itching and flaking due to dandruff

Warnings

For external use only

When using this product

- avoid contact with eyes. If contact occurs, rinse eyes thoroughly with water.

Stop use and consult a doctor

- if condition worsens or does not improve after regular use of this product as directed.

Keep out of reach of children.

If swallowed, get medical help or call a poison control center at once.

Directions

- Spray to apply to the affected areas 1-4 times daily, or as directed by a doctor.

Inactive Ingredients

Water, Glycerin, PEG-12 Dimethicone, Propylene Glycol, Sodium Hydroxide, Hydrolyzed Collagen, Disodium EDTA, Diazolidinyl Urea, Methylparaben, Propylparaben, Benzyl Alcohol, Benzyl Benzoate, Eugenol, Hydroxycitronellal, Linalool, Fragrance.